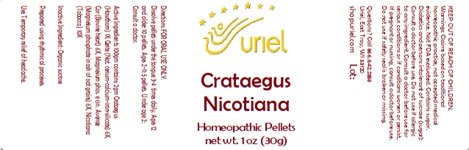 DRUG LABEL: Crataegus Nicotiana
NDC: 48951-3135 | Form: PELLET
Manufacturer: Uriel Pharmacy Inc.
Category: homeopathic | Type: HUMAN OTC DRUG LABEL
Date: 20241025

ACTIVE INGREDIENTS: HAWTHORN LEAF WITH FLOWER 1 [hp_X]/1 1; CERIUM 6 [hp_X]/1 1; BEEF HEART 6 [hp_X]/1 1; MAGNESIUM PHOSPHATE, TRIBASIC, PENTAHYDRATE 6 [hp_X]/1 1; TOBACCO LEAF 10 [hp_X]/1 1
INACTIVE INGREDIENTS: SUCROSE

Crataegus Nicotiana

INDICATIONS AND USAGE

Directions: FOR ORAL USE ONLY.

DOSAGE AND ADMINISTRATION

Dissolve pellets under the tongue 3-4 times daily. Ages 12 and older: 10 pellets. Ages 2-11: 5 pellets. Under age 2: Consult a doctor.

ACTIVE INGREDIENT

Active Ingredients: 100gm contains: 2gm Crataegus (Hawthorn) 1X; Cerite (Nat. cerium-calcium-iron-silicate) 6X, Cor (Bovine heart) 6X, Magnesium phos. e cin. Avenae (Magnesium phosphate in ash of oat grains) 6X, Nicotiana (Tobacco) 10X

Inactive Ingredients: Organic sucrose

Prepared using rhythmical processes

PURPOSE

Use: Temporary relief of headache.

KEEP OUT OF REACH OF CHILDREN.

WARNINGS

Warnings: Claims based on traditional homeopathic practice, not accepted medical evidence. Not FDA evaluated. Contains sugar. Diabetics and persons intolerant of sucrose (sugar): Consult a doctor before use. Do not use if allergic to any ingredient. Consult a doctor before use for serious conditions or if conditions worsen or persist. If pregnant or nursing, consult a doctor before use. Do not use if safety seal is broken or missing.

QUESTIONS

Questions? Call 866.642.2858 Uriel, East Troy, WI 53120 shopuriel.com Lot: